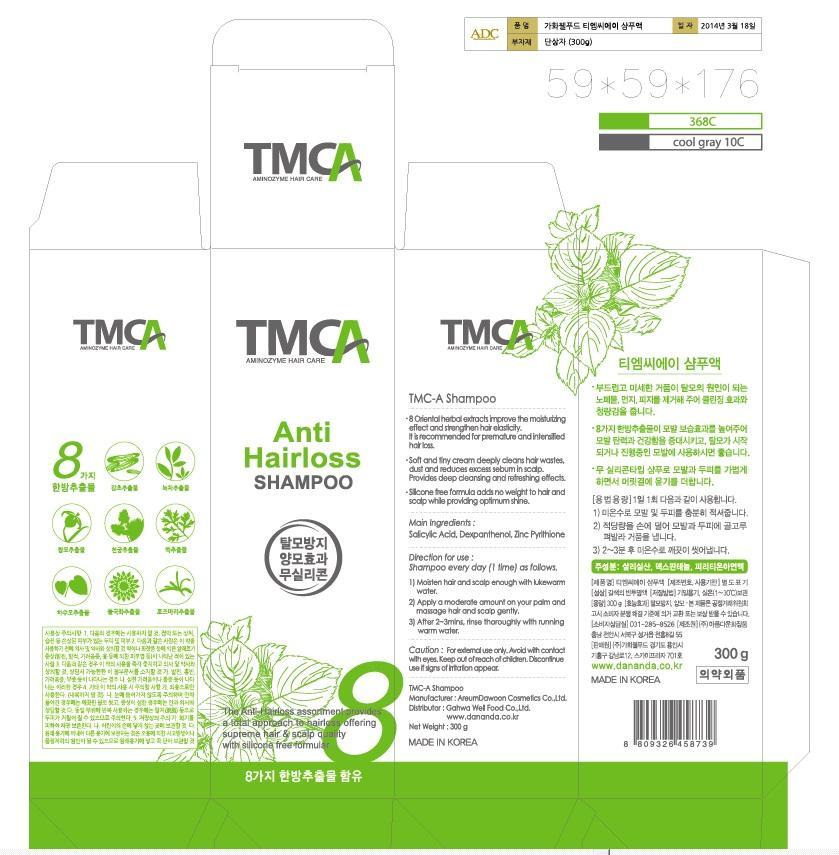 DRUG LABEL: TMC-A Anti Hairloss
NDC: 69100-2001 | Form: SHAMPOO
Manufacturer: Gahwa Well Food Co.,Ltd
Category: otc | Type: HUMAN OTC DRUG LABEL
Date: 20140711

ACTIVE INGREDIENTS: GLYCERIN 2 g/100 g
INACTIVE INGREDIENTS: COCAMIDOPROPYL BETAINE; NIACINAMIDE; METHYLPARABEN

Drug Facts

ACTIVE INGREDIENT

glycerine

INACTIVE INGREDIENT

d.i water, biotin, nicotinamide, d-panthenol, zinc pyrithione liquid (48%), ammonium laureth sulfate (28%), ammonium lauryl sulfate (28%), edta-2na, methyl paraben, cocamide dea, cocamidopropyl betaine, l-menthol, methylchloroisothiazolinone/methylisothiazolinone, triethanolamine, polyquaternium-10, cabomer, eucalyptus ext, licorice root ext, camellia sinensis leaf ext, acorus calamus root ext, cnidium officinale root ext, artemisia vulgaris ext, chrysanthemum morifolium flower ext, rosemary ext, polygonum multiflorum root ext

PURPOSE

for hair grower and hair loss prevention

keep out of reach of the children

INDICATIONS AND USAGE

shampoo everyday (1 time) as follows
1) moisten hair and scalp enough with lukewarm water
2) apply a moderate amount on your palm and massage hair and scalp gently
3) after 2~3 minutes, rinse throughly with running warm water

do not use on damaged or broken skin
when using this product keep out of eyes rinse with water to remove
stop use and ask a doctor if rash occurs
do not swallow

DOSAGE AND ADMINISTRATION

for external use only